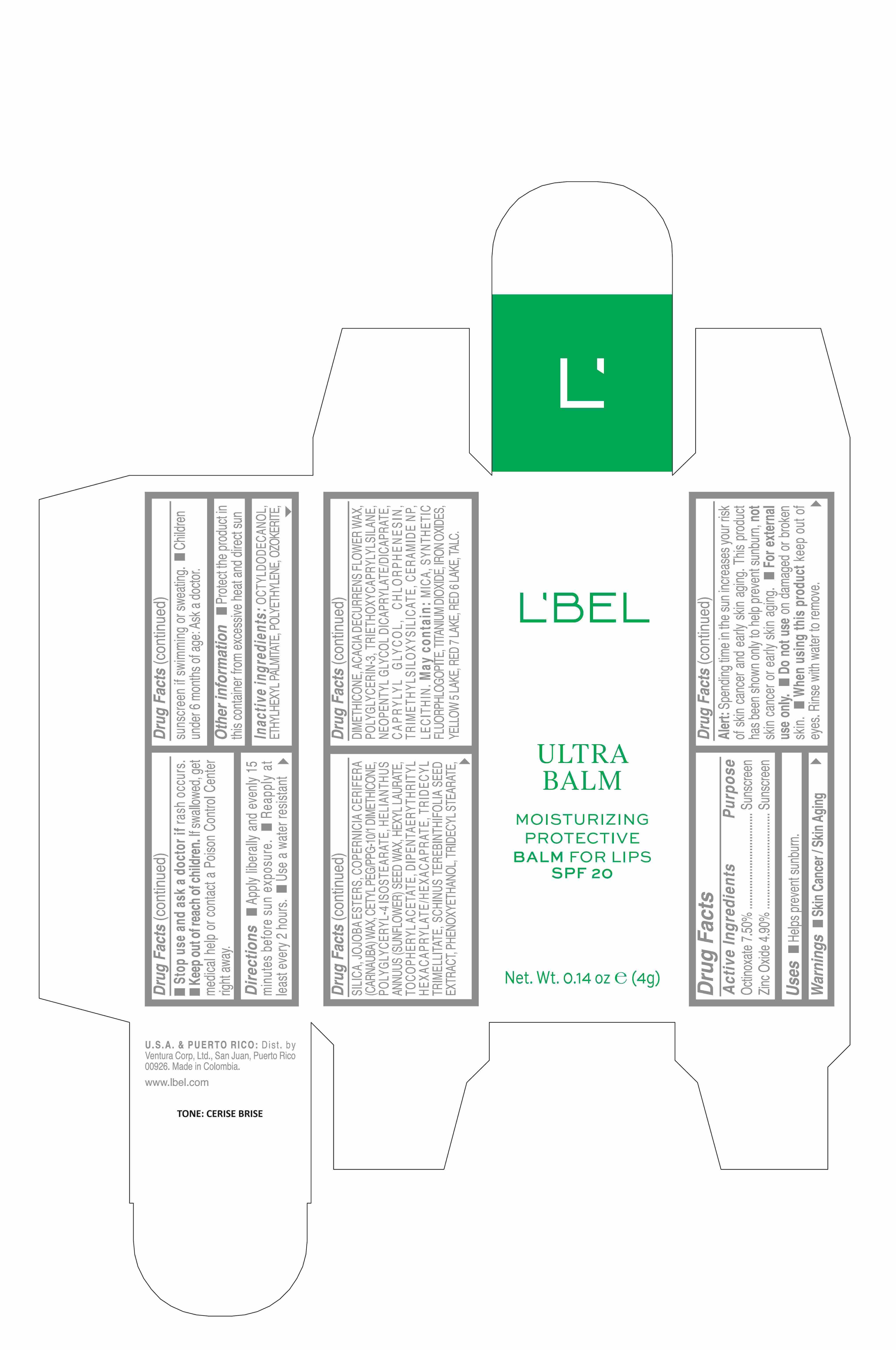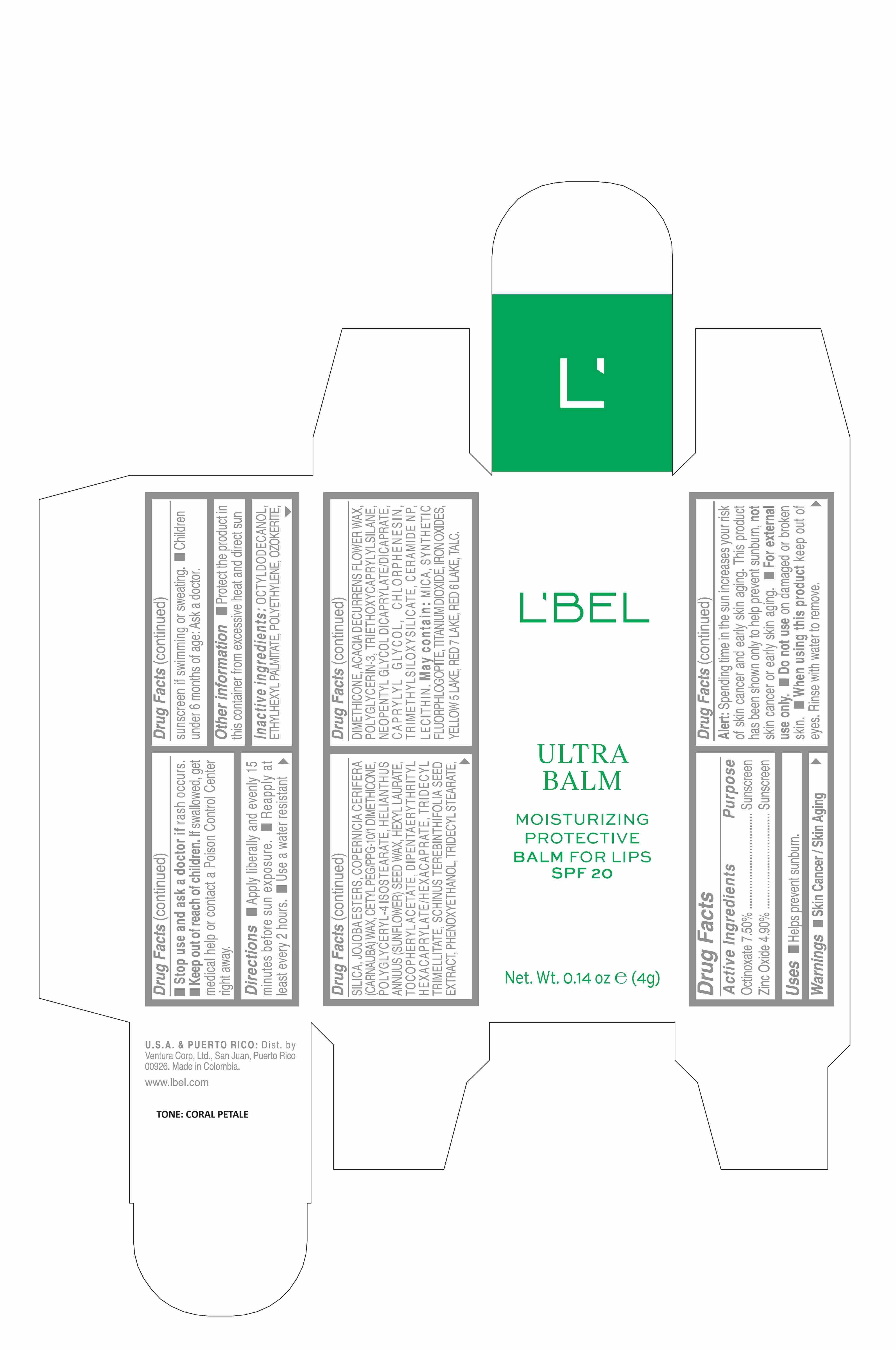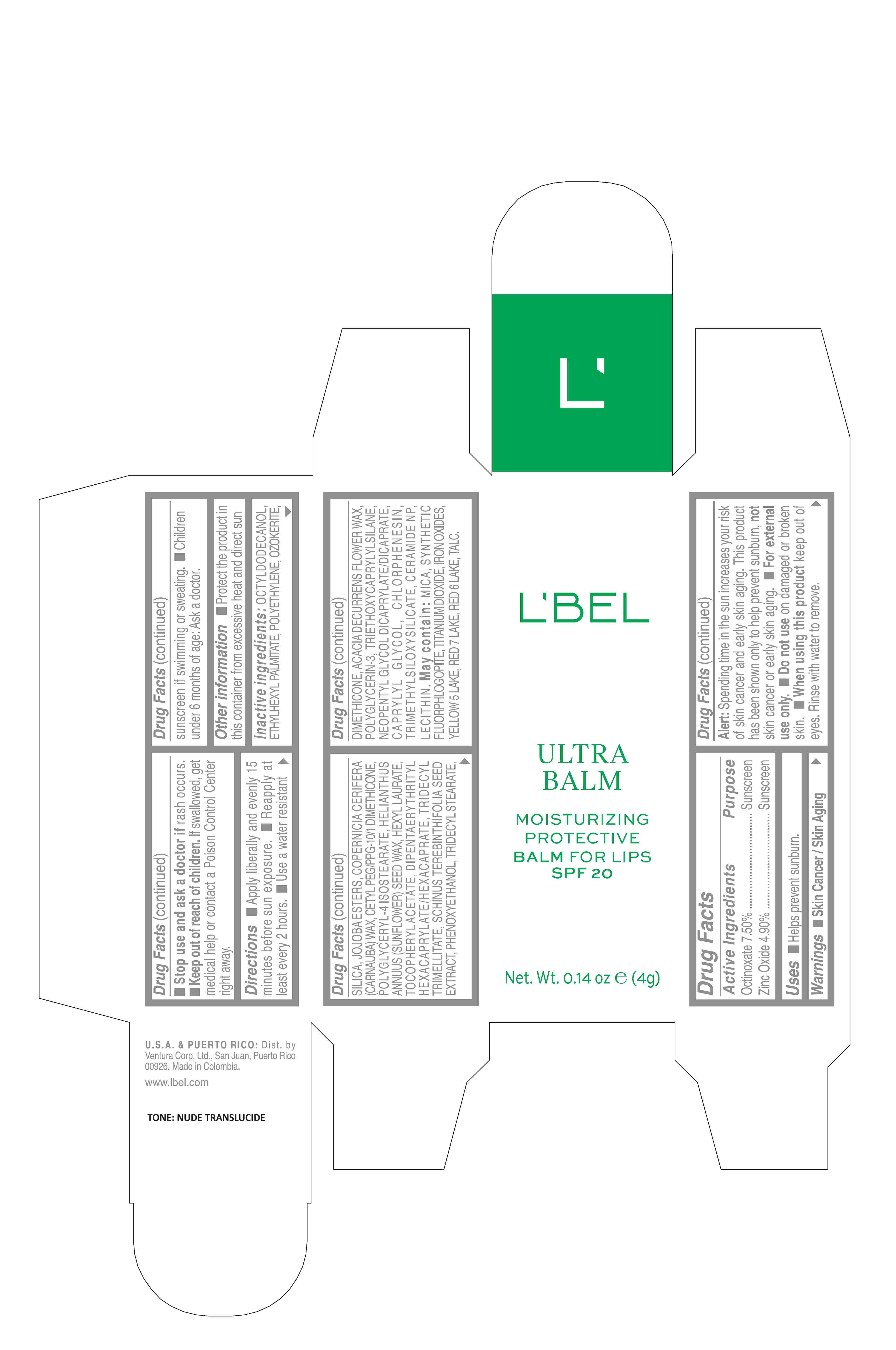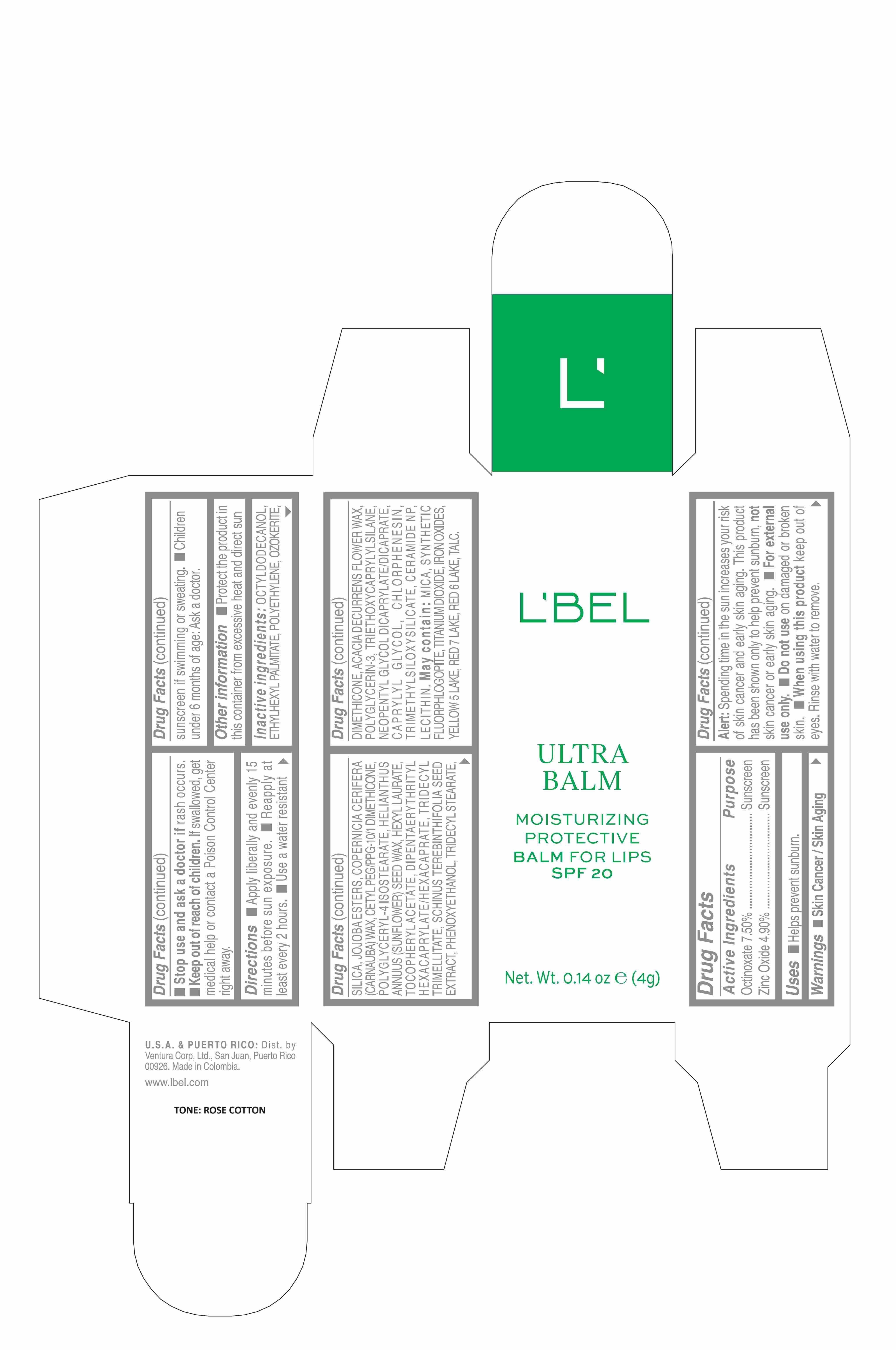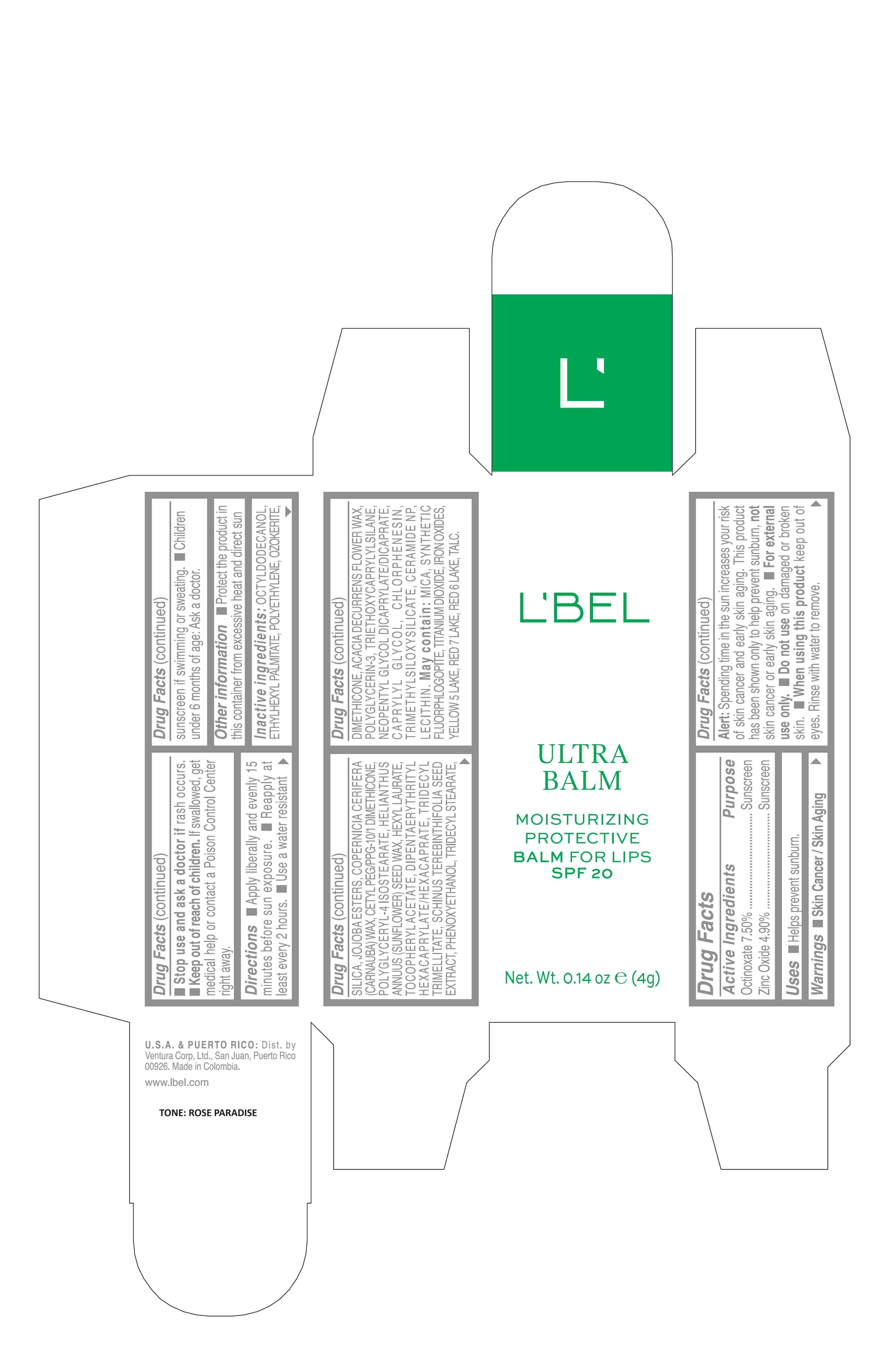 DRUG LABEL: Ultra Balm Moisturizing Protective Balm for lips SPF 20 Coral Petale
NDC: 14141-453 | Form: STICK
Manufacturer: BEL STAR S A
Category: otc | Type: HUMAN OTC DRUG LABEL
Date: 20250619

ACTIVE INGREDIENTS: ZINC OXIDE 4.9 g/100 g; OCTINOXATE 7.5 g/100 g
INACTIVE INGREDIENTS: BRAZILIAN PEPPER; CHLORPHENESIN; NEOPENTYL GLYCOL DICAPRYLATE/DICAPRATE; OCTYLDODECANOL; CARNAUBA WAX; CETYL PEG/PPG-10/1 DIMETHICONE (HLB 1.5); .ALPHA.-TOCOPHEROL ACETATE; HELIANTHUS ANNUUS SEED WAX; HEXYL LAURATE; ACACIA DECURRENS FLOWER WAX; ETHYLHEXYL PALMITATE; DIPENTAERYTHRITYL HEXACAPRYLATE/HEXACAPRATE; TRIDECYL TRIMELLITATE; POLYGLYCERYL-4 ISOSTEARATE; CERESIN; SILICON DIOXIDE; FERROSOFERRIC OXIDE; FERRIC OXIDE YELLOW; HIGH DENSITY POLYETHYLENE; TRIETHOXYCAPRYLYLSILANE; POLYGLYCERIN-3; PHENOXYETHANOL; TRIDECYL STEARATE; DIMETHICONE; CAPRYLYL GLYCOL; TRIMETHYLSILOXYSILICATE (M/Q 0.6-0.8); CERAMIDE NP; LECITHIN, SOYBEAN; MICA; TITANIUM DIOXIDE; MAGNESIUM POTASSIUM ALUMINOSILICATE FLUORIDE; FERRIC OXIDE RED; TALC

Ultra Balm Moisturizing Protective Balm for Lips SPF 20

Active Ingredients Purpose
Octinoxate 7.50%.............Sunscreen
Zinc oxide 4.90 %........... Sunscreen

Uses

- Helps prevent sunburn.

- Keep out of reach of children.If swallowed, get medical help or contact a Poison Control Center right away.

- Stop use and ask a doctor ifrash occurs.

Warnings

- Skin Cancer / Skin Aging Alert:Spending time in the sun increases your risk of skin cancer and early skin aging. This product has been shown only to help prevent sunburn, not skin cancer or early skin aging.
- For external use only.
- Do not useon damaged or broken skin.
- When using this productkeep out of eyes. Rinse with water to remove.

Directions

- Apply liberally and evenly 15 minutes before sun exposure.
- Reapply at least every 2 hours
- Use a water resistant sunscreen if swimming or sweating.
- Children under 6 months of age: Ask a doctor

Other Information

Protect the product in this container from excessive heat and direct sun

INACTIVE INGREDIENT

Inactive ingredients:octyldodecanol, ethylhexyl palmitate, polyethylene, ozokerite, silica, jojoba esters, copernicia cerifera (carnauba) wax, cetyl peg/ppg-10/1 dimethicone, polyglyceryl-4 isostearate, helianthus annuus (sunflower) seed wax, hexyl laurate, tocopheryl acetate, dipentaerythrityl hexacaprylate/hexacaprate, tridecyl trimellitate, schinus terebinthifolia seed extract, phenoxyethanol, tridecyl stearate, dimethicone, acacia decurrens flower wax, polyglycerin-3, triethoxycaprylylsilane, neopentyl glycol dicaprylate/dicaprate, caprylyl glycol, chlorphenesin, trimethylsiloxysilicate, ceramide np, lecithin.
may contain:
mica, titanium dioxide, synthetic fluorphlogopite, iron oxides, yellow 5 lake, red 7 lake, red 6 lake, talc.